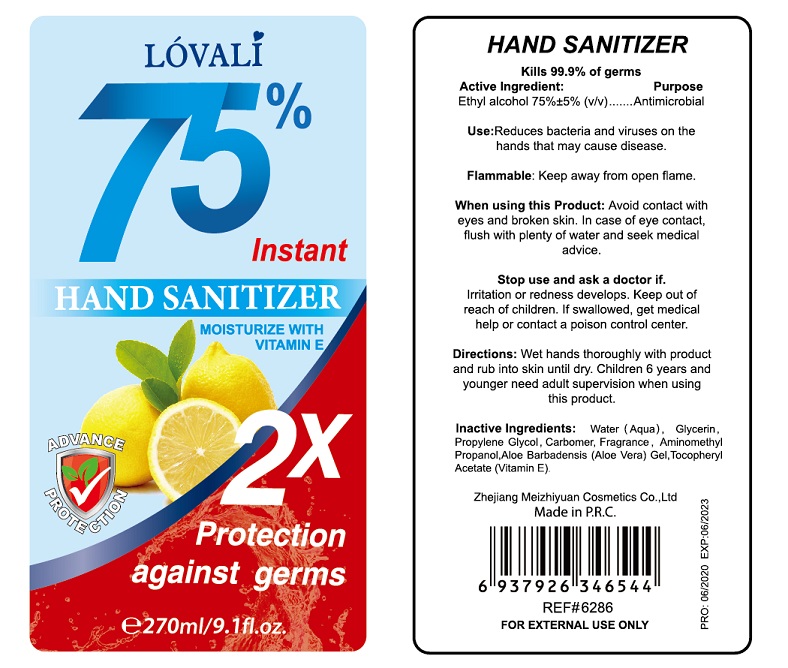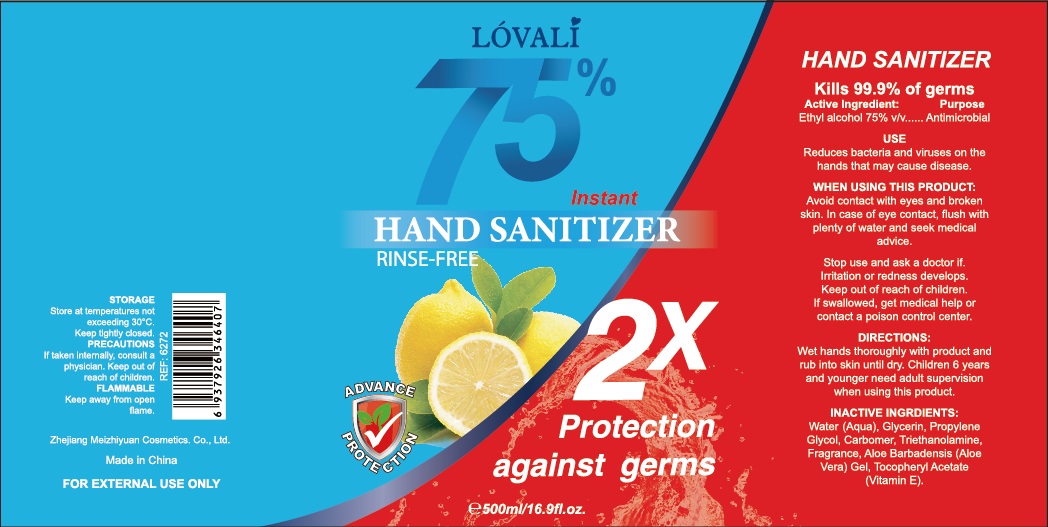 DRUG LABEL: Lovali Hand Sanitizer
NDC: 75007-003 | Form: GEL
Manufacturer: YIRONG TRADING (NANJING) CO., LTD
Category: otc | Type: HUMAN OTC DRUG LABEL
Date: 20200726

ACTIVE INGREDIENTS: ALCOHOL 75 mL/100 mL
INACTIVE INGREDIENTS: WATER; GLYCERIN; PROPYLENE GLYCOL; CARBOMER HOMOPOLYMER TYPE A (ALLYL PENTAERYTHRITOL CROSSLINKED); AMINOMETHYLPROPANOL; ALOE VERA LEAF; .ALPHA.-TOCOPHEROL ACETATE, D-

Active Ingredient

Ethyl Alcohol 75% ± 5 % v/v.

Purpose

Antimicrobial

Use

Reduces bacteria and viruses on the hands that may cause disease.

Warnings

Flammable. Keep away from open flame.

When using this Product: Avoid contact with eyes and broken skin. In case of eye contact, flush with plenty of water and seek medical advice.

Stop use and ask a doctor if irritation or redness develops.

Keep out of reach of children. If swallowed, get medical help or contact a Poison Control Center right away.

Directions

Wet hands thoroughly with product and rub into skin until dry.

Children 6 years and younger need adult supervision when using this product.

Inactive ingredients

Water (Aqua). Glycerin, Propylene Glycol, Carbomer, Fragrance, Aminomethyl Propanol,Aloe Barbadensis (Aloe Vera) Gel,Tocopheryl Acetate (Vitamin E)